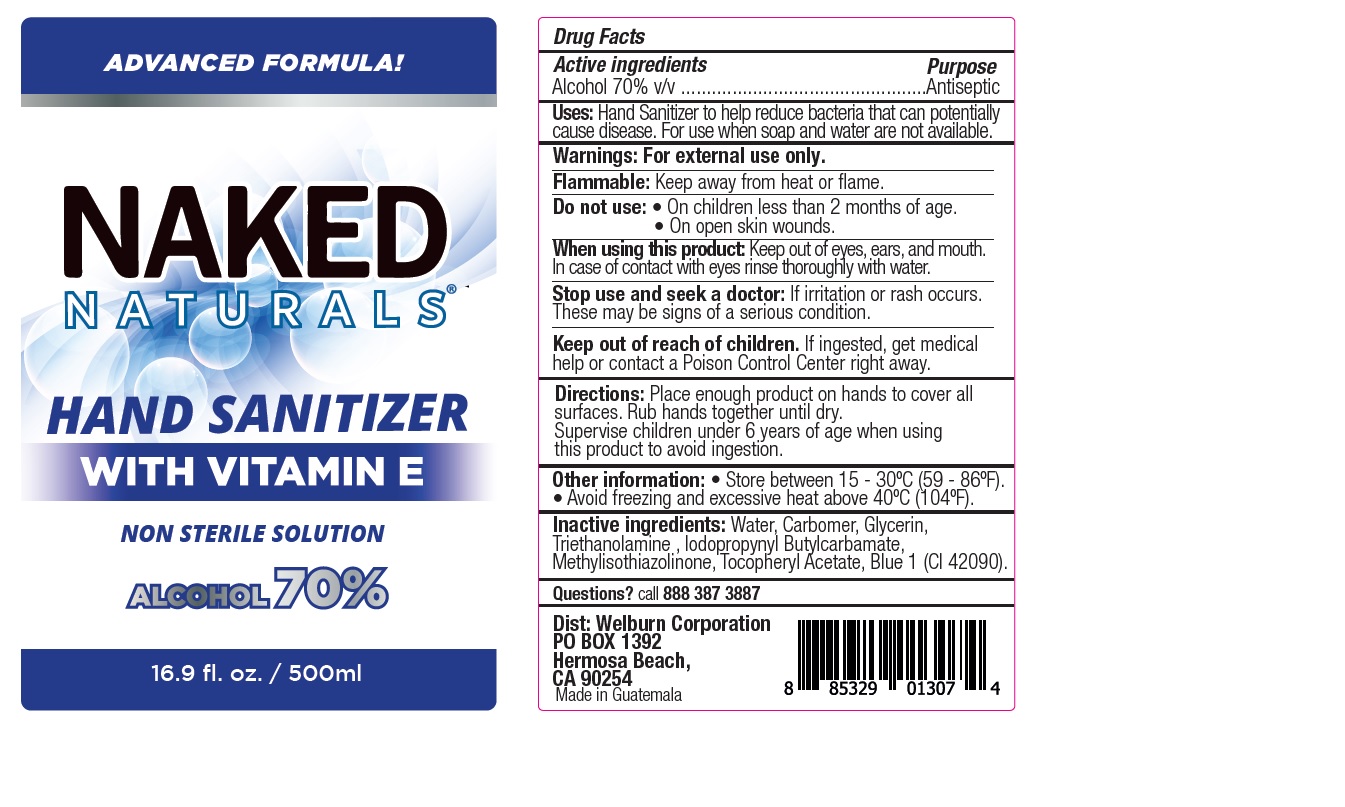 DRUG LABEL: NAKED NATURALS HAND SANITIZER WITH VITAMIN E
NDC: 77622-007 | Form: GEL
Manufacturer: Welburn Corporation
Category: otc | Type: HUMAN OTC DRUG LABEL
Date: 20200625

ACTIVE INGREDIENTS: ALCOHOL 70 mL/100 mL
INACTIVE INGREDIENTS: GLYCERIN; CARBOMER HOMOPOLYMER, UNSPECIFIED TYPE; METHYLISOTHIAZOLINONE; IODOPROPYNYL BUTYLCARBAMATE; TROLAMINE; WATER; .ALPHA.-TOCOPHEROL ACETATE; FD&C BLUE NO. 1

Hand Sanitizer with Vitamin E - Welburn Corporation

Active ingredients

Alcohol 70% v/v

Purpose

Antiseptic

Uses

Hand Sanitizer to help reduce bacteria that can potentially cause disease. For use when soap and water are not available.

Warnings

For external use only.

Flammable. Keep away from heat or flame.

Do not use

- On children less than 2 months of age.
- On open skin wounds.

When using this product

Keep out of eyes, ears and mouth. In case of contact with eyes rinse thoroughly with water.

Stop use and seek a doctor

If irritation or rash occurs. These may be signs of a serious condition.

Keep out of reach of children.

If ingested, get medical help or contact a Poison Control Center right away.

Directions

Place enough product on hands to cover all surfaces. Rub hands together until dry.

Supervise children under 6 years of age when using this product to avoid ingestion.

Other information

- Store between 15-30C (59-86F).
- Avoid freezing and excessive heat above 40C (104F).

Inactive ingredients

Water, Carbomer, Glycerin, Triethanolamine, Iodopropynyl Butylcarbamate, Methylisothiazolinone, Tocopheryl Acetate, Blue 1 (CI 42090).

Questions?

call 888 387 3887

Company Information

Dist: Welburn Corporation

PO BOX 1392

Hermosa Beach, CA 90254

Made in Guatemala

Product Packaging - 500ml

ADVANCED FORMULA!

NAKED

NATURALS

HAND SANITIZER

WITH VITAMIN E

NON STERILE SOLUTION

ALCOHOL 70%

16.9 fl. oz. / 500ml